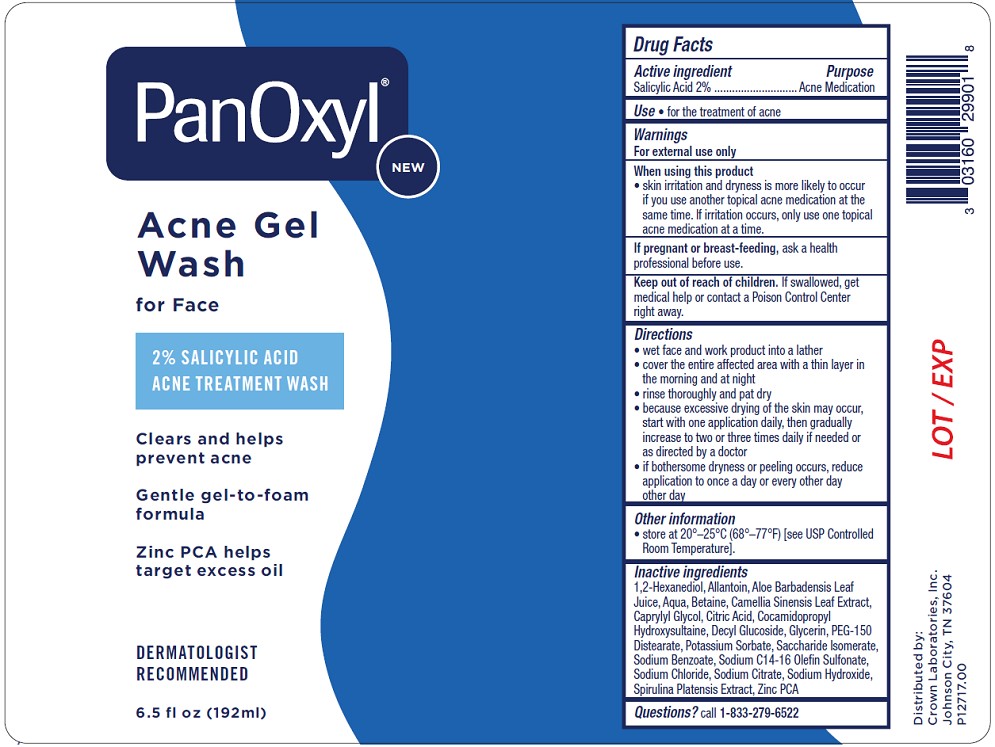 DRUG LABEL: PanOxyl Acne Gel Wash
NDC: 0316-0299 | Form: GEL
Manufacturer: Crown Laboratories, Inc.
Category: otc | Type: HUMAN OTC DRUG LABEL
Date: 20260112

ACTIVE INGREDIENTS: SALICYLIC ACID 2 g/100 mL
INACTIVE INGREDIENTS: 1,2-HEXANEDIOL; GREEN TEA LEAF; CAPRYLYL GLYCOL; DECYL GLUCOSIDE; SACCHARIDE ISOMERATE; SODIUM CITRATE; GLYCERIN; POTASSIUM SORBATE; BETAINE; CITRIC ACID; SODIUM CHLORIDE; SPIRULINA PLATENSIS; WATER; SODIUM BENZOATE; ALOE BARBADENSIS LEAF JUICE; COCAMIDOPROPYL HYDROXYSULTAINE; PEG-150 DISTEARATE; SODIUM HYDROXIDE; SODIUM C14-16 OLEFIN SULFONATE; ZINC PCA; ALLANTOIN

PanOxyl Acne Gel Wash

Active ingredient

Salicylic Acid 2%

Purpose

Acne Medication

Use

- for the treatment of acne

Warnings

For external use only

When using this product

- skin irritation and dryness is more likely to occur if you use another topical acne medication at the same time. If irritation occurs, only use one topical acne medication at a time.

If pregnant or breast-feeding,

ask a health professional before use.

Keep out of reach of children.

If swallowed, get medical help or contact a Poison Control Center right away.

Directions

- wet face and work product into a lather
- cover the entire affected area with a thin layer in the morning and at night
- rinse thoroughly and pat dry
- because excessive drying of the skin may occur, start with one application daily, then gradually increase to two or three times daily if needed or as directed by a doctor
- if bothersome dryness or peeling occurs, reduce application to once a day or every other day other day

Other information

- Store at 20o - 25oC (68o - 77oF) [see USP Controlled Room Temperature].

Inactive ingredients

1,2-Hexanediol, Allantoin, Aloe Barbadensis Leaf Juice, Aqua, Betaine, Camellia Sinensis Leaf Extract, Caprylyl Glycol, Citric Acid, Cocamidopropyl Hydroxysultaine, Decyl Glucoside, Glycerin, PEG-150 Distearate, Potassium Sorbate, Saccharide Isomerate, Sodium Benzoate, Sodium C14-16 Olefin Sulfonate, Sodium Chloride, Sodium Citrate, Sodium Hydroxide, Spirulina Platensis Extract, Zinc PCA

Questions?

call 1-833-279-6522

PanOxyl Acne Gel Wash Label

NEW

PanOxyl

Acne Gel Wash

for Face

2% SALICYLIC ACID

ACNE TREATMENT WASH

Clears and helps prevent acne

Gentle gel-to-foam formula

Zinc PCA helps target excess oil

DERMATOLIGST RECOMMENDED

6.5 fl oz (192ml)

Distributed by: Crown Laboratories, Inc.

Johnson City, TN 37604

P12717.00